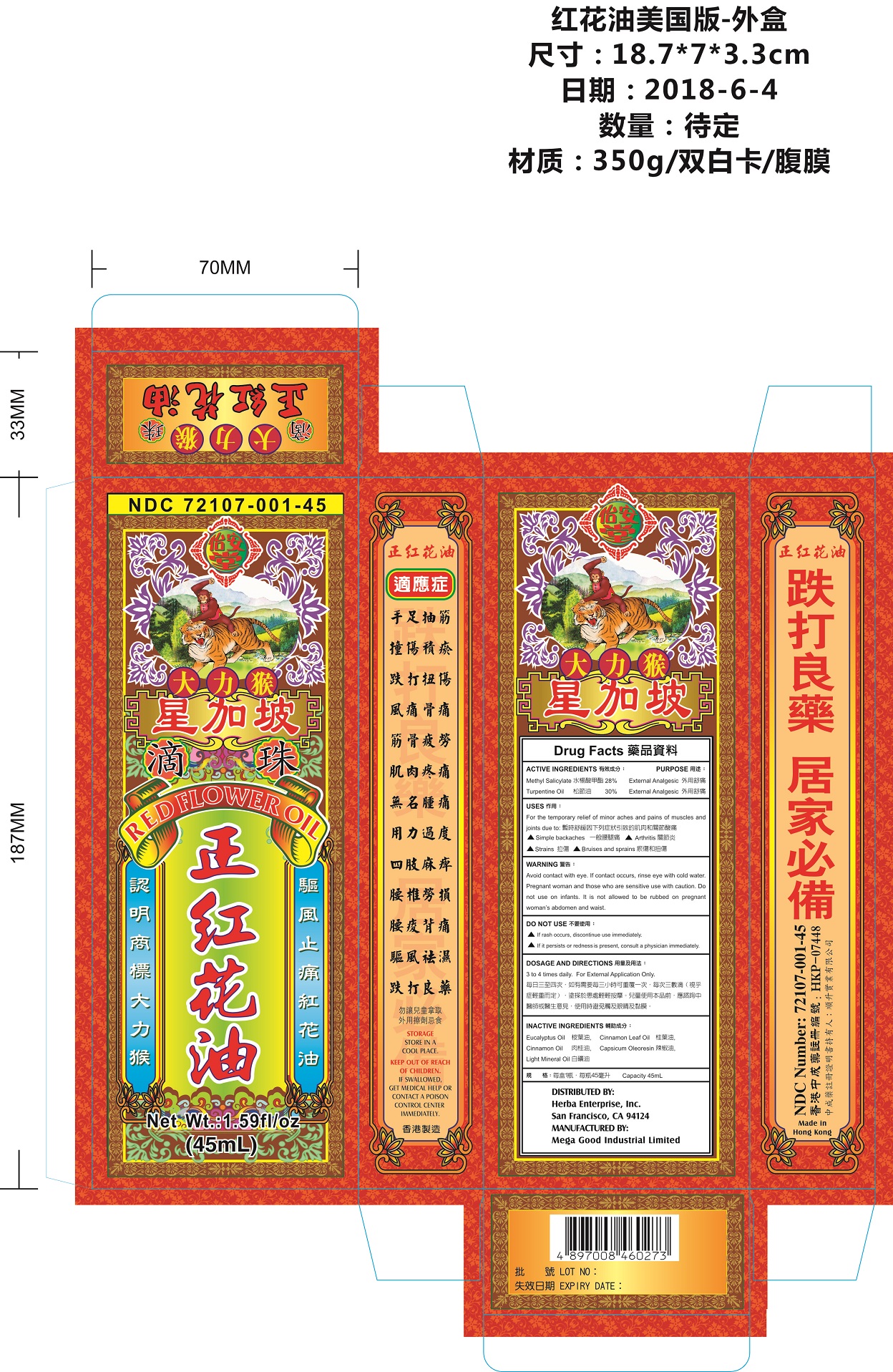 DRUG LABEL: Red Flower Oil
NDC: 72107-001 | Form: OIL
Manufacturer: Mega Good Industrial Limited
Category: otc | Type: HUMAN OTC DRUG LABEL
Date: 20180906

ACTIVE INGREDIENTS: METHYL SALICYLATE 28 g/100 mL; TURPENTINE 30 g/100 mL
INACTIVE INGREDIENTS: EUCALYPTUS OIL; CINNAMON LEAF OIL; CINNAMON OIL; CAPSICUM OLEORESIN; LIGHT MINERAL OIL

Mega Good Industrial Limited

Active Ingredients

Methyl Salicylate 28% External Analgesic
Turpentine Oil 30% External Analgesic

Uses

For the temporary relief of minor aches and pains of muscles and joints due to: simple backaches, arthritis, strains, bruises and sprains.

Directions

For External Application Only.

Dosage

3 to 4 times daily.

Warning

Avoid contact with eye. If contact occurs, rinse eye with cold water. Pregnant woman and those who are sensitive, use with caution. Do not use on infants. It is not allowed to be rubbed on pregnant woman’s abdomen and waist.

Keep out of reach of children. If swallowed, get medical help or contact a Poison Control Center immediately.

Do not Use

If rash occurs, discontinue use immediately. If it persists or redness is present, consult a physician immediately.

Storage

Store in a cool place.

Manufactured by

Mega Good Industrial Limited

Made in Hong Kong

Inactive Ingredients

EUCALYPTUS OIL, CINNAMON LEAF OIL, CINNAMON OIL, CAPSICUM OLEORESIN, LIGHT MINERAL OIL